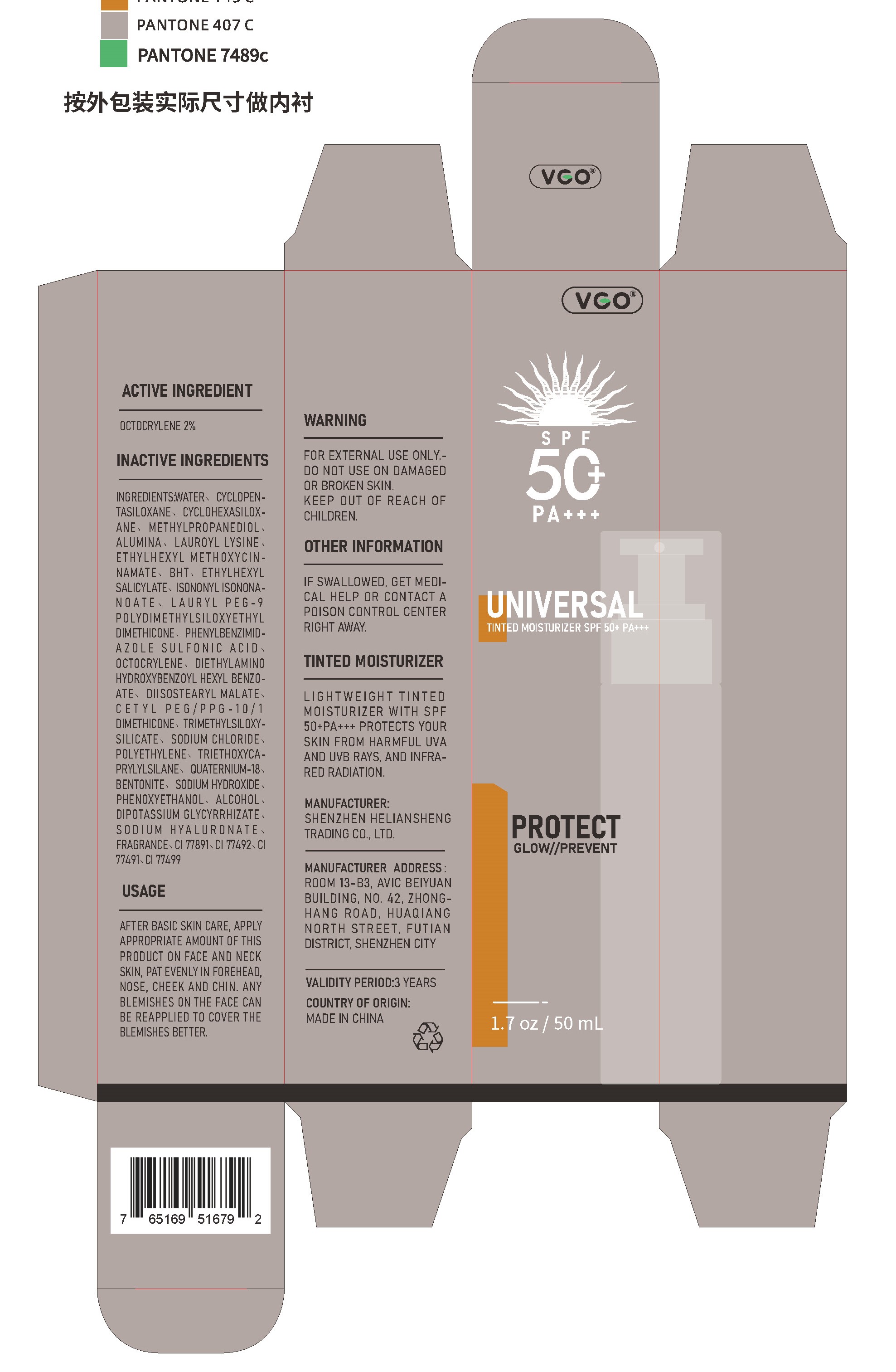 DRUG LABEL: VCO UV CLEAR SUNSCREEN
NDC: 84191-001 | Form: OINTMENT
Manufacturer: Shenzhen Heliansheng Trading Co., Ltd.
Category: otc | Type: HUMAN OTC DRUG LABEL
Date: 20240325

ACTIVE INGREDIENTS: OCTOCRYLENE 1 g/50 g
INACTIVE INGREDIENTS: SODIUM HYDROXIDE; PHENOXYETHANOL; OCTINOXATE; BUTYLATED HYDROXYTOLUENE; DIETHYLAMINO HYDROXYBENZOYL HEXYL BENZOATE; DIISOSTEARYL MALATE; CYCLOMETHICONE 5; LAUROYL LYSINE; ISONONYL ISONONANOATE; TRIMETHYLSILOXYSILICATE (M/Q 0.6-0.8); ALUMINUM OXIDE; OCTISALATE; TRIETHOXYCAPRYLYLSILANE; FERRIC OXIDE YELLOW; CYCLOMETHICONE 6; METHYLPROPANEDIOL; LAURYL PEG-9 POLYDIMETHYLSILOXYETHYL DIMETHICONE; ENSULIZOLE; CETYL PEG/PPG-10/1 DIMETHICONE (HLB 2); SODIUM CHLORIDE; BENTONITE; GLYCYRRHIZINATE DIPOTASSIUM; HYALURONATE SODIUM; TITANIUM DIOXIDE; FERROSOFERRIC OXIDE; WATER; HIGH DENSITY POLYETHYLENE; QUATERNIUM-18; ALCOHOL; FERRIC OXIDE RED

84191-001

Active ingredient

Octocrylene 2%

Purpose

Sunscreen

Use

helps prevent sunburn

higher SPF gives more sunburn protection

Warning

For external use only.

Do not use

on damaged or broken skin.

If Swallowed

Get medical help or contact a poison control center right away.

Directions

After Basic Skin Care, Apply Appropriate Amount Of This Product On Face And Neck Skin, Pat Evenly In Forehead, Nose, Cheek And Chin. Any Blemishes On The Face Can Be Reapplied To Cover The Blemishes Better.

Inactive ingredients

WATER、CYCLOPENTASILOXANE、CYCLOHEXASILOXANE、METHYLPROPANEDIOL、ALUMINA、LAUROYL LYSINE、ETHYLHEXYL METHOXYCINNAMATE、BHT、ETHYLHEXYL SALICYLATE、ISONONYL ISONONANOATE、LAURYL PEG-9 POLYDIMETHYLSILOXYETHYL DIMETHICONE、PHENYLBENZIMIDAZOLE SULFONIC ACID、DIETHYLAMINO HYDROXYBENZOYL HEXYL BENZOATE、DIISOSTEARYL MALATE、CETYL PEG/PPG-10/1 DIMETHICONE、TRIMETHYLSILOXYSILICATE、SODIUM CHLORIDE、POLYETHYLENE、TRIETHOXYCAPRYLYLSILANE、QUATERNIUM-18、BENTONITE、SODIUM HYDROXIDE、PHENOXYETHANOL、ALCOHOL、DIPOTASSIUM GLYCYRRHIZATE、SODIUM HYALURONATE、FRAGRANCE、CI 77891、CI 77492、CI 77491、CI 77499